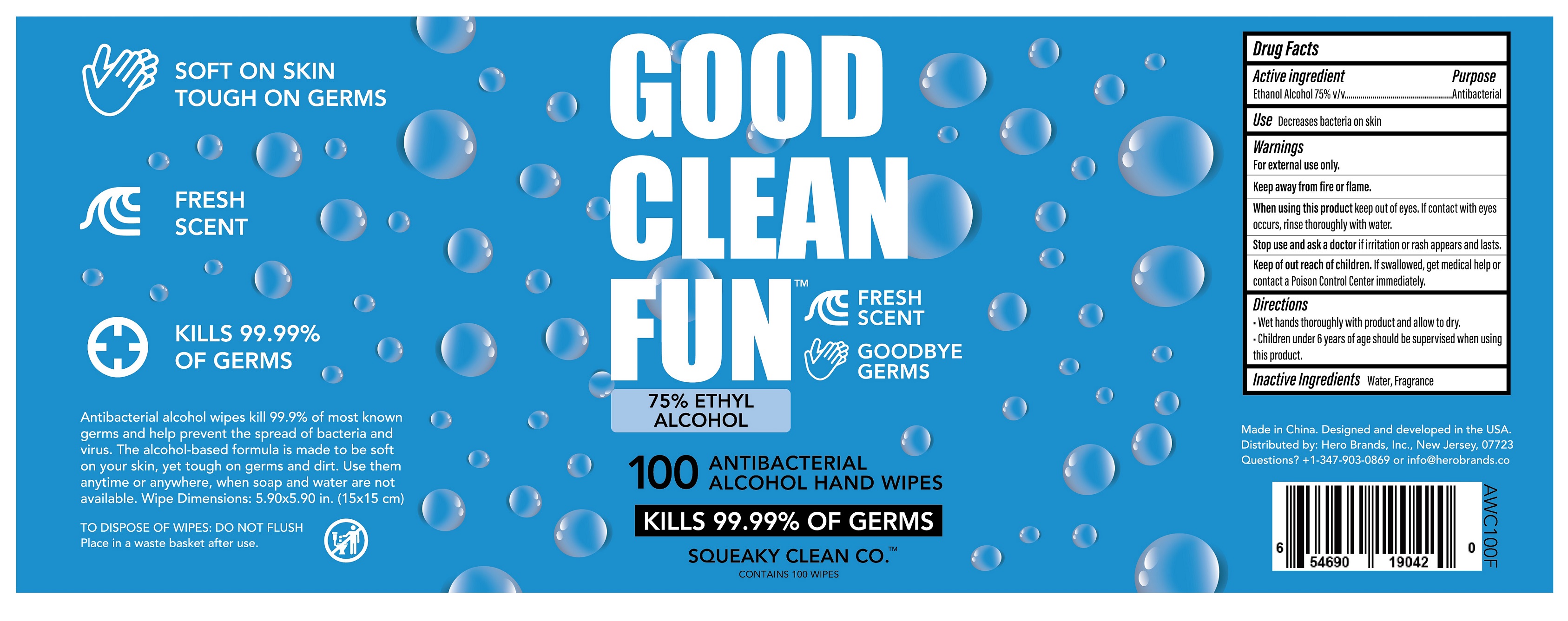 DRUG LABEL: 100 Canister Alcohol Wipes - Fresh Scent
NDC: 90114-401 | Form: CLOTH
Manufacturer: Hero Brands, Inc.
Category: otc | Type: HUMAN OTC DRUG LABEL
Date: 20200923

ACTIVE INGREDIENTS: ALCOHOL 75 mL/100 mL
INACTIVE INGREDIENTS: LAVENDER OIL; WATER

90114-401-02 100 Canister Alcohol Wipes - Fresh Scent jianhe 20200923 75163-011

Active Ingredient(s)

Ethanol Alcohol 75% v/v. Purpose: Antibacterial

Purpose

Antibacterial

Use

Decreases bacteria on skin.

Warnings

- For external use only.
- Keep away from fire or flame

When using

When using this product keep out of eyes. If contact with eyes occurs, rinse thoroughly with water.

Stop use and ask a doctor if irritation or rash appears and lasts.

Keep out of reach of children. If swallowed, get medical help or contact a Poison Control Center immediately.

Directions

- Wet hands thoroughly with product and allow to dry.
- Children under 6 years of age should be supervised when using product.

Other information

- Store between 15-30C (59-86F)
- Avoid freezing and excessive heat above 40C (104F)

Inactive ingredients

Water, Fragrance.

Package Label - Principal Display Panel

100 CLOTH IN 1 CONISTER NDC: 90114-401-02